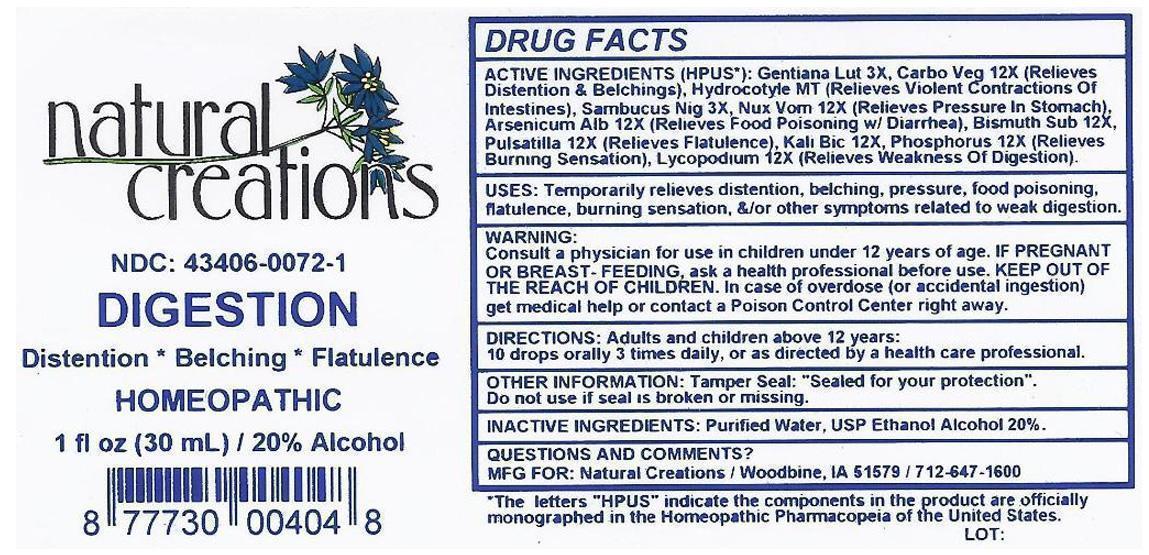 DRUG LABEL: DIGESTION
NDC: 43406-0072 | Form: LIQUID
Manufacturer: Natural Creations, Inc.
Category: homeopathic | Type: HUMAN OTC DRUG LABEL
Date: 20130129

ACTIVE INGREDIENTS: CENTELLA ASIATICA 1 [hp_X]/1 mL; GENTIANA LUTEA ROOT 3 [hp_X]/1 mL; SAMBUCUS NIGRA FLOWERING TOP 3 [hp_X]/1 mL; Arsenic Trioxide 12 [hp_X]/1 mL; BISMUTH SUBNITRATE 12 [hp_X]/1 mL; ACTIVATED CHARCOAL 12 [hp_X]/1 mL; POTASSIUM DICHROMATE 12 [hp_X]/1 mL; LYCOPODIUM CLAVATUM SPORE 12 [hp_X]/1 mL; STRYCHNOS NUX-VOMICA SEED 12 [hp_X]/1 mL; PHOSPHORUS 12 [hp_X]/1 mL; PULSATILLA VULGARIS 12 [hp_X]/1 mL
INACTIVE INGREDIENTS: WATER; ALCOHOL

DIGESTION

ACTIVE INGREDIENT

ACTIVE INGREDIENTS (HPUS*): Hydrocotyle Asiatice MT, Gentiana Lutea 3X, Sambucus Nigra 3X, Arsenicum Album 12X, Bismuthum Subnitricum 12X, Carbo Vegetabilis 12X, Kali Bichromicum 12X, Lycopodium Clavatum 12X, Nux Vomica 12X, Phosphorus 12X, Pulsatilla 12X

PURPOSE

USES: Temporily relieves distention, belching, pressure, food poisoning, flatulence, burning sensation, &/or other symptoms related to weak digestion.

KEEP OUT OF REACH OF CHILDREN. In case of overdose (or accidential ingestion) get medical help or contact a Poison Control Center.

INDICATIONS AND USAGE

USES: Temporarily relieves distention, belching, pressure, food poisoning, flatulence, burning sensation, &/or other symptoms related to weak digestion.

WARNING:

Consult a physician forn use in children under 12 years of age. IF PREGNANT OR BREAST FEEDING, ask a health care professional before use. KEEP OUT OF THE REACH OF CHILDREN. In case of overdose (or accidential ingestion) get medical help or contact a Poison Control Center right away.

DOSAGE AND ADMINISTRATION

DIRECTIONS: Adults and children above 12 yeares: 10 drops orally 3 times daily or as directed by a health care professional.

INACTIVE INGREDIENTS: Purified Water, USP Ethanol Alcohol 20%

PACKAGE LABEL

NDC: 43406-0072-1

DIGESTION

Distention*Belching*Flatulence

HOMEOPATHIC

1 fl oz (30 mL) / 20% Alcohol

UPC: 877730004048